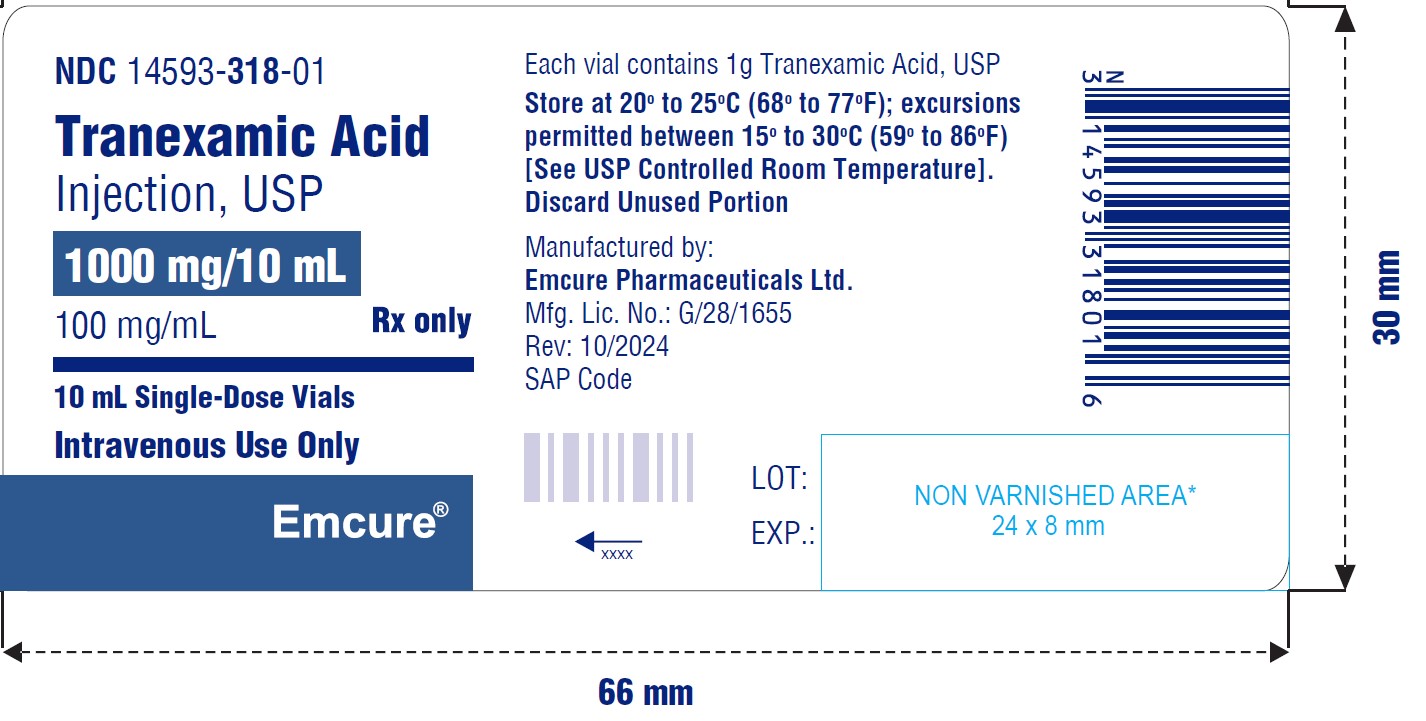 DRUG LABEL: Tranexamic Acid
NDC: 14593-318 | Form: INJECTION, SOLUTION
Manufacturer: Emcure Pharmaceuticals Limited
Category: prescription | Type: HUMAN PRESCRIPTION DRUG LABEL
Date: 20241028

ACTIVE INGREDIENTS: TRANEXAMIC ACID 1 g/10 mL
INACTIVE INGREDIENTS: WATER

Rx only

INDICATIONS AND USAGE

Tranexamic acid injection, USP is indicated in patients with hemophilia for short-term use (2 to 8 days) to reduce or prevent hemorrhage and reduce the need for replacement therapy during and following tooth extraction.

PACKAGE LABEL.PRINCIPAL DISPLAY PANEL

NDC 14593-318-01

Tranexamic Acid Injection, USP

1000 mg/10 mL

(100 mg/mL)

Intravenous Use Only

Rx only

10 mL Single-Dose Vial